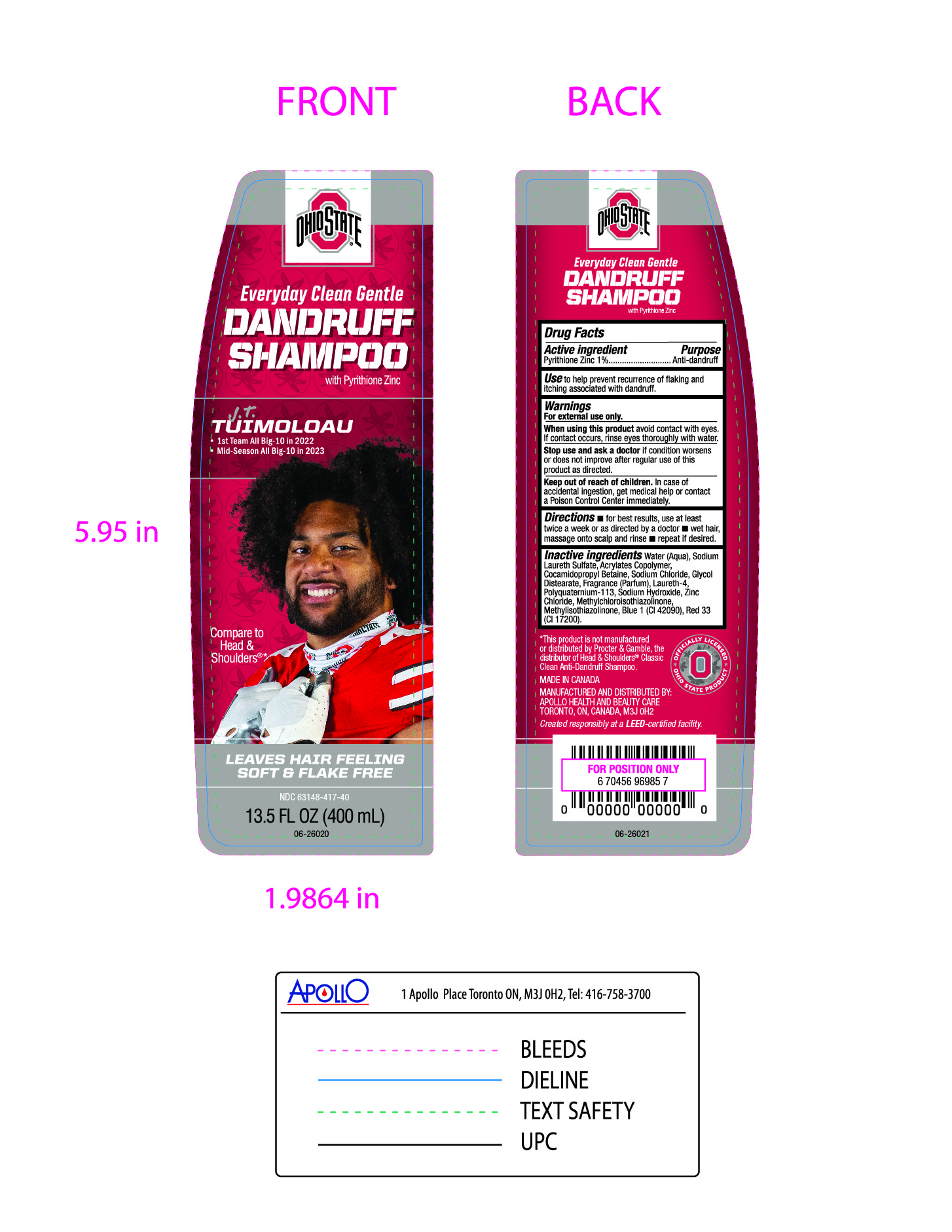 DRUG LABEL: Everyday Clean
NDC: 63148-417 | Form: SHAMPOO
Manufacturer: Apollo Health and Beauty Care
Category: otc | Type: HUMAN OTC DRUG LABEL
Date: 20231127

ACTIVE INGREDIENTS: PYRITHIONE ZINC 10 mg/1 mL
INACTIVE INGREDIENTS: COCAMIDOPROPYL BETAINE; D&C RED NO. 33; WATER; SODIUM LAURETH SULFATE; GLYCOL DISTEARATE; METHACRYLIC ACID - METHYL METHACRYLATE COPOLYMER (1:1); SODIUM HYDROXIDE; ZINC CHLORIDE; METHYLCHLOROISOTHIAZOLINONE; ACRYLATES/VINYL ISODECANOATE CROSSPOLYMER (10000 MPA.S NEUTRALIZED AT 0.5%); METHYLISOTHIAZOLINONE; DIRECT BLUE 1; FRAGRANCE CLEAN ORC0600327; LAURETH-4; SODIUM CHLORIDE

Ohio State Everyday Clean Gentle Dandruff Shampoo

Active Ingredient

Pyrithione Zinc 1%

Purpose

Anti-dandruff

Use

To help prevent recurrence of flaking and itching associated with dandruff.

Warnings

For external use only.

When using this product

avoid contact with eyes. If contact occurs, rinse eyes throughly with water.

Stop use and ask a doctor

if condition worsens or does not improve after regular use of this product as directed.

Keep out of reach of children

In case of accidental ingestion, get medical help or contact a Poison Control Center immediately.

Directions

- For Best results, use at least twice a week or as directed by a doctor.
- Wet hair, massage onto scalp and rinse.
- repeat if desired.

Inactive Ingredients

Water (Aqua), Sodium Laureth Sulfate, Acrylates Copolymer, Cocamidopropyl Betaine, Sodium Chloride, Glycol Distearate, Fragrance (Parfum), Laureth-4, Polyquaternium-113, Sodium Hydroxide, Zinc Chloride, Methylchloroisothiazolinone, Methylisothiazolinone, Blue 1 (CL 42090), Red 33 (Cl 17200.